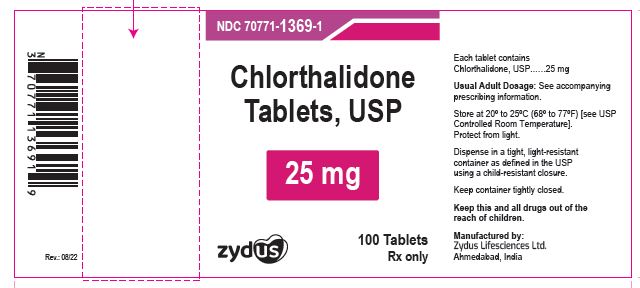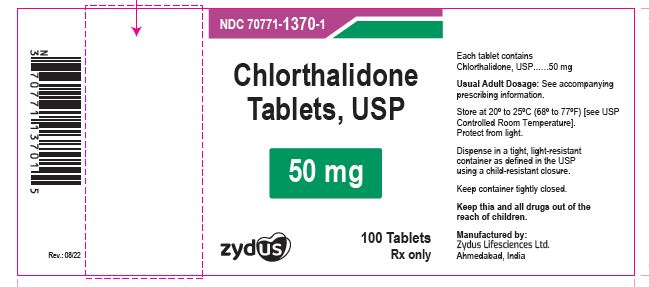 DRUG LABEL: Chlorthalidone
NDC: 70771-1369 | Form: TABLET
Manufacturer: Zydus Lifesciences Limited
Category: prescription | Type: HUMAN PRESCRIPTION DRUG LABEL
Date: 20241126

ACTIVE INGREDIENTS: CHLORTHALIDONE 25 mg/1 1
INACTIVE INGREDIENTS: CELLULOSE, MICROCRYSTALLINE; FERRIC OXIDE YELLOW; SILICON DIOXIDE; SODIUM STARCH GLYCOLATE TYPE A POTATO; STARCH, CORN; STEARIC ACID

Chlorthalidone Tablets, USP

PACKAGE LABEL.PRINCIPAL DISPLAY PANEL

NDC 70771-1369-1

Chlorthalidone tablets USP ,25 mg

Rx only

100 tablets

NDC 70771-1370-1

Chlorthalidone tablets USP, 50 mg

Rx only

100 tablets